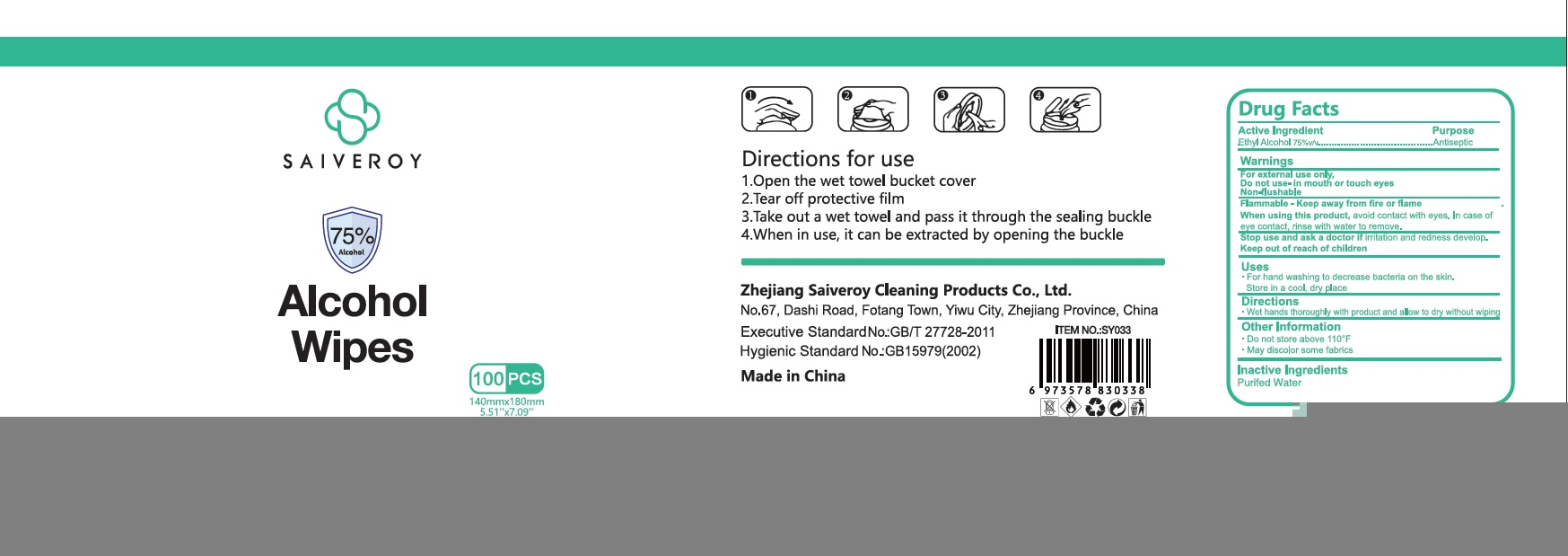 DRUG LABEL: Saiveroy Alcohol Wipes
NDC: 79680-002 | Form: SWAB
Manufacturer: Zhejiang Saiveroy Cleaning Products Co., LTD.
Category: otc | Type: HUMAN OTC DRUG LABEL
Date: 20200728

ACTIVE INGREDIENTS: ALCOHOL 75 g/100 g
INACTIVE INGREDIENTS: WATER

Wipes

Active Ingredient

Ethyl Alcohol 75%

Purpose

Antiseptic

USE

For hand washing to decrease bacteria on the skin.

Store in a cool, dry place

Warning

- Flammable, keep away from fire or flame.
- For external use only. Do not use -in mouth or touch eyes. Non-fushable.
- When using this product, avoid contact with eyes. In case of eye contact, rinse with water to remove.

- Stop use and ask a doctor, f irritaion and redness develop

Other information

Do not store above 110℉

May discolor some fabrics.

KEEP OUT OF REACH OF CHILDREN

●If swallowed, get medical help or contact a Poison Contrl Center right away.

Directions

- Wet hands thoroughluy with produt and allow to dry without wiping.

Inactive ingredients

Purifed Water